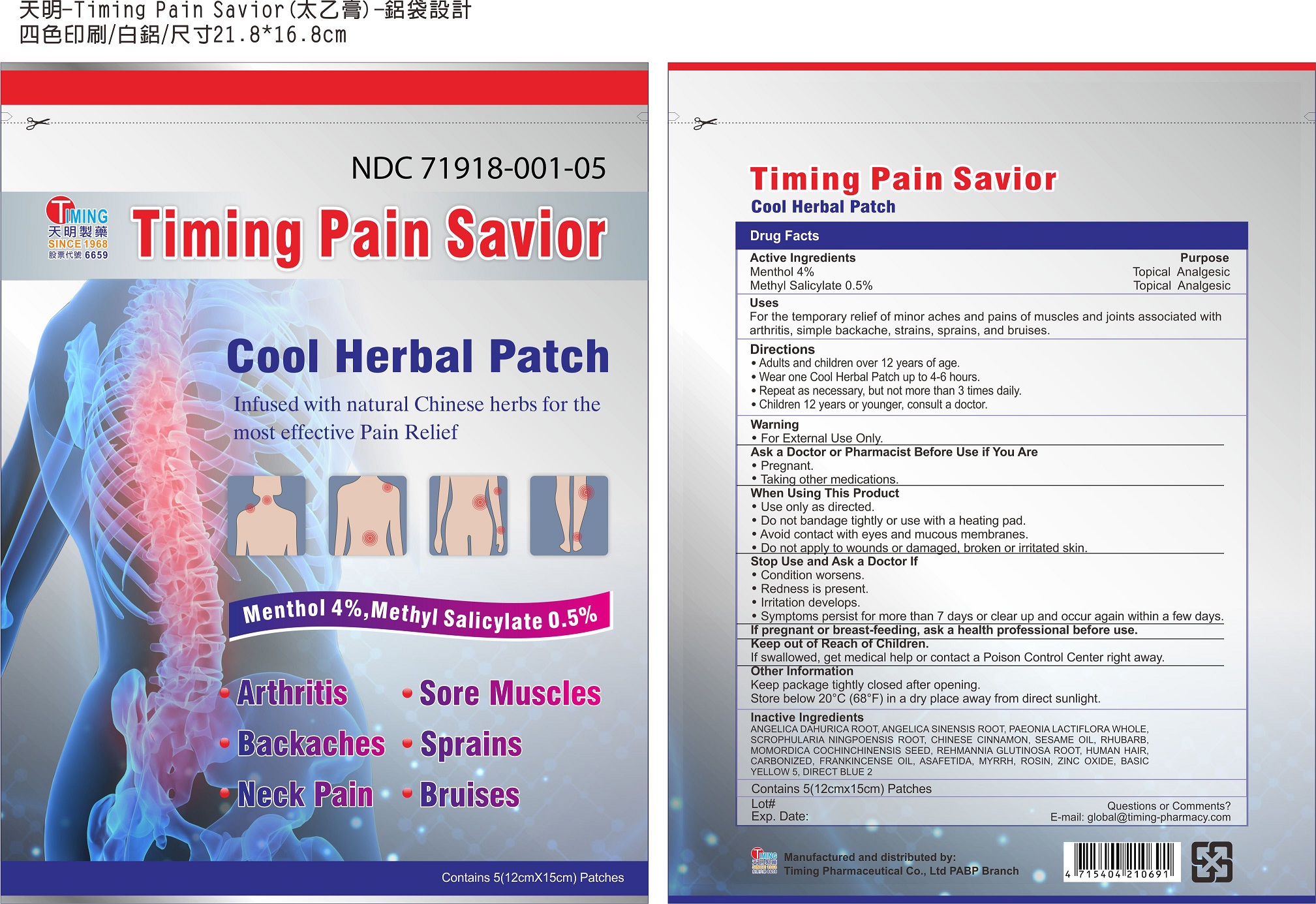 DRUG LABEL: Timing Pain Savior Cool Herbal Patch
NDC: 71918-001 | Form: PATCH
Manufacturer: Timing Pharmaceutical Co., Ltd PABP Branch
Category: otc | Type: HUMAN OTC DRUG LABEL
Date: 20260114

ACTIVE INGREDIENTS: MENTHOL 4 g/100 g; METHYL SALICYLATE 0.5 g/100 g
INACTIVE INGREDIENTS: ANGELICA DAHURICA ROOT; ANGELICA SINENSIS ROOT; PAEONIA LACTIFLORA WHOLE; SCROPHULARIA NINGPOENSIS ROOT; CHINESE CINNAMON; SESAME OIL; RHUBARB; MOMORDICA COCHINCHINENSIS SEED; REHMANNIA GLUTINOSA ROOT; HUMAN HAIR, CARBONIZED; FRANKINCENSE OIL; ASAFETIDA; MYRRH; ROSIN; ZINC OXIDE; BASIC YELLOW 5; DIRECT BLUE 2

Timing Pharmaceutical Co., Ltd PABP Branch

Active Ingredients

Menthol 4%

Methyl Salicylate 0.5%

Purpose

Menthol Topical Analgesic

Methyl Salicylate Topical Analgesic

Uses

For the temporary relief of minor aches and pains of muscles and joints associated with arthritis, simple backache, strains, sprains, and bruises.

Directions

Adults and children over 12 years of age.

Wear one Cool Herbal Patch up to 4-6 hours.

Repeat as necessary, but not more than 3 times daily.

Children 12 years or younger, consult a doctor.

Warning

For External Use Only.

Ask a Doctor or Pharmacist Before Use if You Are

pregnant.

taking other medications.

When Using This Product

Use only as directed.

Do not bandage tightly or use with a heating pad.

Avoid contact with eyes and mucous membranes.

Do not apply to wounds or damaged, broken or irritated skin.

Stop Use and Ask a Doctor If

condition worsens.

redness is present.

irritation develops.

symptoms persist for more than 7 days or clear up and occur again within a few days.

Keep out of reach of children.

If swallowed, get medical help or contact a Poison Control Center right away.

Other Information

Keep package tightly closed after opening.

Store below 20℃ (68 ℉) in a dry place away from direct sunlight.

Questions or Comments?

E-mail: global@timing-pharmacy.com

Inactive Ingredients

ANGELICA DAHURICA ROOT, ANGELICA SINENSIS ROOT, PAEONIA LACTIFLORA WHOLE, SCROPHULARIA NINGPOENSIS ROOT, CHINESE CINNAMON, SESAME OIL, RHUBARB, MOMORDICA COCHINCHINENSIS SEED, REHMANNIA GLUTINOSA ROOT, CARBONIZED HUMAN HAIR, FRANKINCENSE OIL, ASAFETIDA, MYRRH, ROSIN, ZINC OXIDE, BASIC YELLOW 5, DIRECT BLUE 2